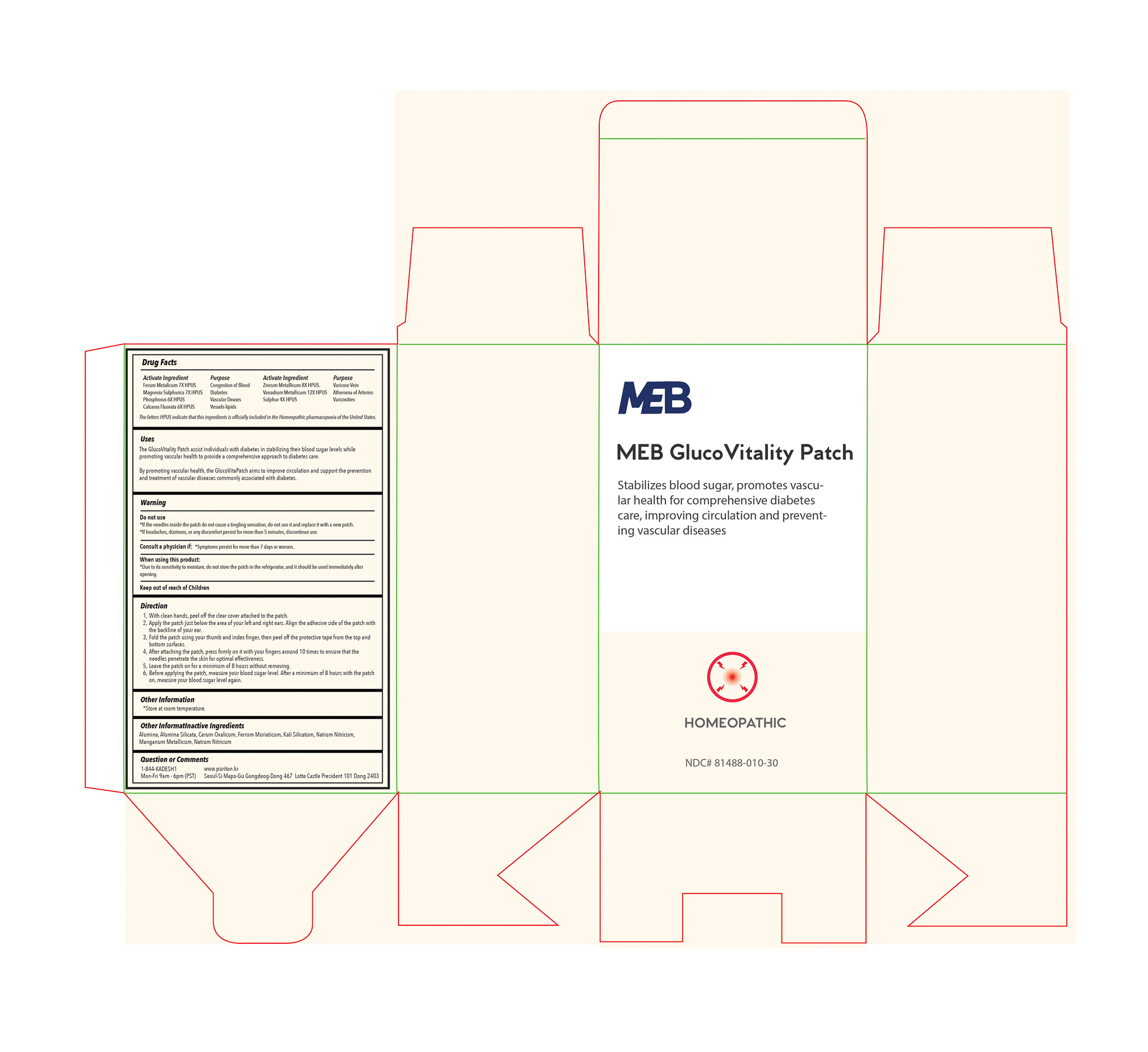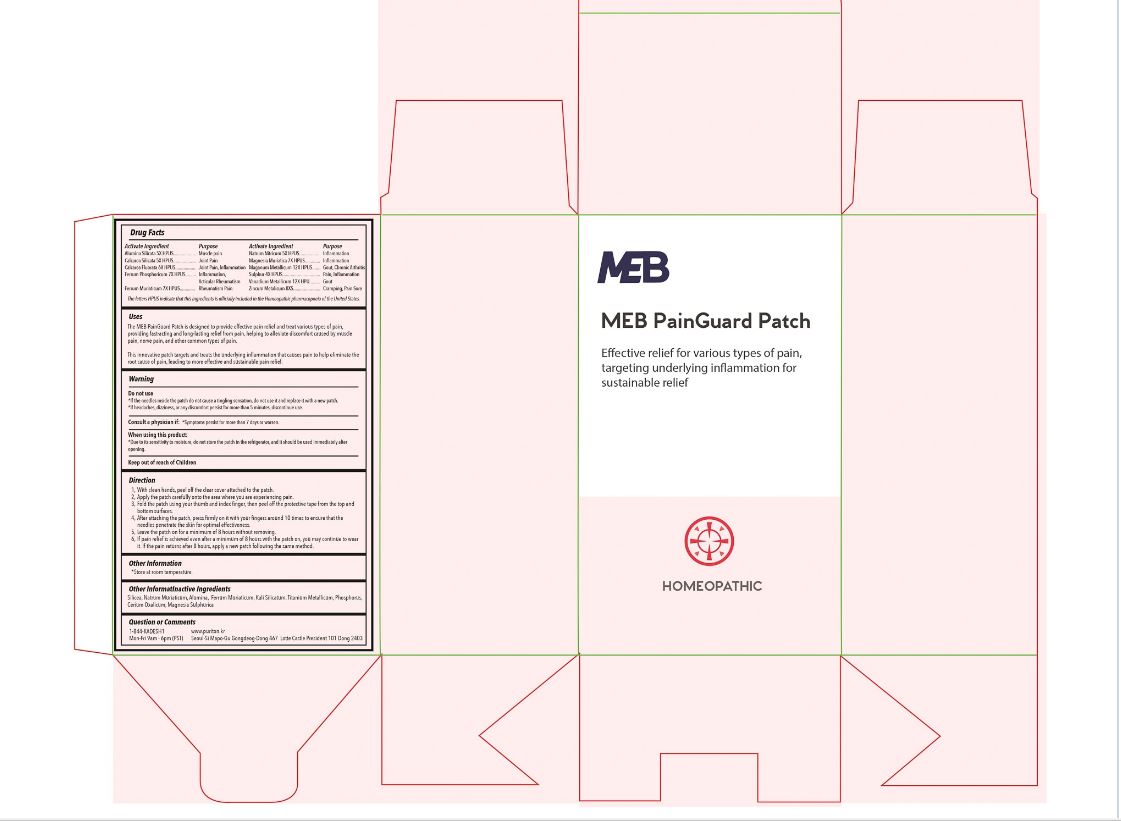 DRUG LABEL: MEB PainGuard Patch
NDC: 81488-011 | Form: PATCH
Manufacturer: Kadesh Incoporation Co,Ltd
Category: homeopathic | Type: HUMAN OTC DRUG LABEL
Date: 20230818

ACTIVE INGREDIENTS: CALCIUM SILICATE 5 [hp_X]/12 [hp_X]; MANGANESE 12 [hp_X]/12 [hp_X]; FERRIC CHLORIDE HEXAHYDRATE 7 [hp_X]/12 [hp_X]; SODIUM NITRATE 5 [hp_X]/12 [hp_X]; FERROSOFERRIC PHOSPHATE 7 [hp_X]/12 [hp_X]; CALCIUM FLUORIDE 6 [hp_X]/12 [hp_X]; KAOLIN 5 [hp_X]/12 [hp_X]; VANADIUM 12 [hp_X]/12 [hp_X]; ZINC 8 [hp_X]/12 [hp_X]; MAGNESIUM CHLORIDE 7 [hp_X]/12 [hp_X]; SULFUR 4 [hp_X]/12 [hp_X]
INACTIVE INGREDIENTS: MAGNESIUM SULFATE HEPTAHYDRATE; CEROUS OXALATE NONAHYDRATE; SILICON DIOXIDE; SODIUM CHLORIDE; POTASSIUM SILICATE; TITANIUM; ALUMINUM OXIDE; PHOSPHORUS

Do not Use

*If the needles inside the patch do not cause a tingling sensation, do not use it and replace it with a new patch.

*If headaches, dizziness, or any discomfort persist for more than 5 minutes, discontinue use.

Consult a physician if: *Symptoms persist for more than 7 days or worsen.

When using this product:

*Due to its sensitivity to moisture, do not store the patch in the refrigerator, and it should be used immediately after opening.

Keep out of reach of Children

ASK DOCTOR

Consult a physician if: *Symptoms persist for more than 7 days or worsen.

INACTIVE INGREDIENT

MEB PainGuard Patch
Silicea, Natrum Muriaticum, Alumina, Ferrum Muriaticum, Kali Silicatum, Titanium Metallicum, Phosphorus. Cerium Oxalicum, Magnesia Sulphurica

MEB Gluco-Vitality Patch

Alumina, Alumina Silicata, Cerum Oxalicum, Ferrum Muriaticum, Kali Silicatum, Natrum Nitricum, Manganum Metallicum, Natrum Nitricum

ACTIVE INGREDIENT

MEB PainGuard Patch

Alumina Silicata , Calcarea Silicata, Calcarea Fluorata, Ferrum Phosphoricum, Ferrum Muriaticum, Natrum Nitricum, Magnesia Muriatica, Maganum Metallicum, Sulphur, Vanadium Metallicum, Zincum Metalicum
MEB Gluco-Vitality Patch
Ferum Metalicum, Magnesia Sulphurica, Phosphorus, Calcarea Fluorata, Zincum Metallicum, Vanadium Metallicum, Sulphur

PURPOSE

MEB Gluco-Vitality Patch
Active Ingredients Purpose

Ferum Metalicum 7X HPUS …………………… Congestion of Blood

Magnesia Sulphurica 7X HPUS ……………….. Diabetes

Phosphorus 6X HPUS …………………………… Vascular Deases

Calcarea Fluorata 6X HPUS …………………… Vessels-lipids

Zincum Metallicum 8X HPUS ………………….. Varicose Vein

Vanadium Metallicum 12X HPUS……………….. Atheroma of Arteries

Sulphur 4X HPUS…………………………………. Varicosities

MEB PainGuard Patch

Active Ingredient ................................................ Purpose
Alumina Silicata 5X HPUS.………………………. Muscle Pain

Calcarea Silicata 5X HPUS………………..…….. Joint Pain

Calcarea Fluorata 6X HPUS……………………. Joint Pain, Inflammation

Ferrum Phosphoricum 7X HPUS.………………. Inflammation, Articular Rheumatism

Ferrum Muriaticum 7X HPUS…………………… Rheumatism Pain

Natrum Nitricum 5X HPUS……………………… Inflammation

Magnesia Muriatica 7X HPUS…………………. Inflammation

Maganum Metallicum 12X HPUS……………… Gout, Chronic Arthritis

Sulphur 4X HPUS………………………………… Pain, Inflammation

Vanadium Metallicum 12X HPUS………………. Gout

Zincum Metalicum 8X …………………………….. Cramping, Pain, Sore

DOSAGE AND ADMINISTRATION

MEB Painguard Patch

Direction

1. With clean hands, peel off the clear cover attached to the patch.
2. Apply the patch carefully onto the area where you are experiencing pain.
3. Fold the patch using your thumb and index finger, then peel off the protective tape from the top and bottom surfaces.
4. After attaching the patch, press firmly on it with your fingers around 10 times to ensure that the needles penetrate the skin for optimal effectiveness.
5. Leave the patch on for a minimum of 8 hours without removing.

If pain relief is achieved even after a minimum of 8 hours with the patch on, you may continue to wear it. If the pain returns after 8 hours, apply a new patch following the same method.
MEB Gluco-Vitality Patch
Direction

Use 2 patch at a time

1. With clean hands, peel off the clear cover attached to the patch.
2. Apply the patches just below the area of your left and right ears. Align the adhesive side of the patch with the backline of your ear.
3. Fold the patch using your thumb and index finger, then peel off the protective tape from the top and bottom surfaces.
4. After attaching the patch, press firmly on it with your fingers around 10 times to ensure that the needles penetrate the skin for optimal effectiveness.
5. Leave the patch on for a minimum of 8 hours without removing.
6. Before applying the patch, measure your blood sugar level. After a minimum of 8 hours with the patch on, measure your blood sugar level again.

INDICATIONS AND USAGE

The MEB PainGuard Patch is designed to provide effective pain relief and treat various types of pain, providing fast-acting and long-lasting relief from pain, helping to alleviate discomfort caused by muscle pain, nerve pain, and other common types of pain.

This innovative patch targets and treats the underlying inflammation that causes pain to help eliminate the root cause of pain, leading to more effective and sustainable pain relief.

The Gluco Vitality Patch assists individuals with diabetes in stabilizing their blood sugar levels while promoting vascular health to provide a comprehensive approach to diabetes care.

By promoting vascular health, the GlucoVitaPatch aims to improve circulation and support the prevention and treatment of vascular diseases commonly associated with diabetes.

RECENT MAJOR CHANGES

INDICATIONS & USAGE
Added

The Gluco Vitality Patch INDICATIONS & USAGE
DOSAGE & ADMINISTRATION
Added
The Gluco Vitality Patch DOSAGE & ADMINISTRATION

PACKAGE LABEL

MEB Gluco-Vitality Patch, NDC: 81488-010-30
MEB PainGuard Patch, NDC: 81488-011-30